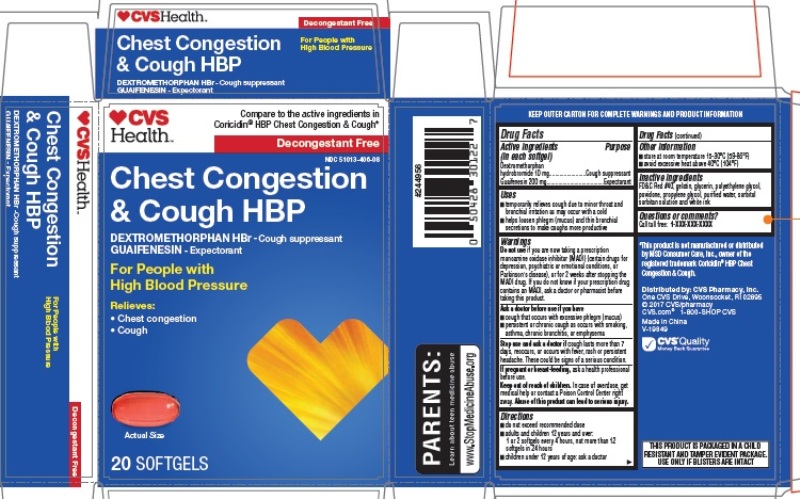 DRUG LABEL: Chest Congestion and Cough HBP
NDC: 51013-406 | Form: CAPSULE, LIQUID FILLED
Manufacturer: PuraCap Pharmaceutical LLC
Category: otc | Type: HUMAN OTC DRUG LABEL
Date: 20200103

ACTIVE INGREDIENTS: DEXTROMETHORPHAN HYDROBROMIDE 10 mg/1 1; GUAIFENESIN 200 mg/1 1
INACTIVE INGREDIENTS: FD&C RED NO. 40; GELATIN; GLYCERIN; POLYETHYLENE GLYCOL, UNSPECIFIED; POVIDONE; PROPYLENE GLYCOL; SORBITOL; SORBITAN; WATER

Chest Congestion & Cough

Active ingredient (in each softgel)

Dextromethorphan hydrobromide 10 mg

Guaifenesin 200 mg

Purpose

Cough suppressant

Expectorant

Uses

- temporarily relieves cough due to minor throat and bronchial irritation as may occur with a cold
- helps loosen phlegm (mucus) and thin bronchial secretions to make coughs more productive

Warnings

Do not use if you are now taking a prescription monoamine oxidase inhibitor (MAOI) (certain drugs for depression, psychiatric or emotional conditions, or Parkinson's disease), or for 2 weeks after stopping the MAOI drug. If you do not know if your prescription drug contains an MAOI, ask a doctor or pharmacist before taking this product.

Ask a doctor before use if you have

- cough that occurs with excessive phlegm (mucus)
- persistent or chronic cough as occurs with smoking, asthma, chronic bronchitis, or emphysema

Stop use and ask a doctor if cough lasts more than 7 days, reoccurs, or occurs with fever, rash or persistent headache. These could be signs of a serious condition.

PREGNANCY OR BREAST FEEDING

If pregnant or breast-feeding, ask a health professional before use.

Keep out of reach of children. In case of overdose, get medical help or contact a Poison Control Center right away. Abuse of this product can lead to serious injury.

Directions

- do not exceed recommended dose
- adults and children 12 years and over:

1 or 2 softgels every 4 hours, not more than 12 softgels in 24 hours

- children under 12 years of age: ask a doctor

Other information

- store at room temperature 15-30°C (59-86°F)
- avoid excessive heat above 40°C (104°F)

Inactive ingredients

FD&C Red #40, gelatin, glycerin, polyethylene glycol, povidone, propylene glycol, purified water, sorbitol sorbitan solution and white ink

Questions or comments

Call toll free: 1-855-215-8180

Principal Display Panel

CVS Chest Congestion & Cough HBP 20 SOFTGELS

NDC: 51013-406-08

*Compare to the active ingredients in Coricidin® HBP Chest Congestion & Cough